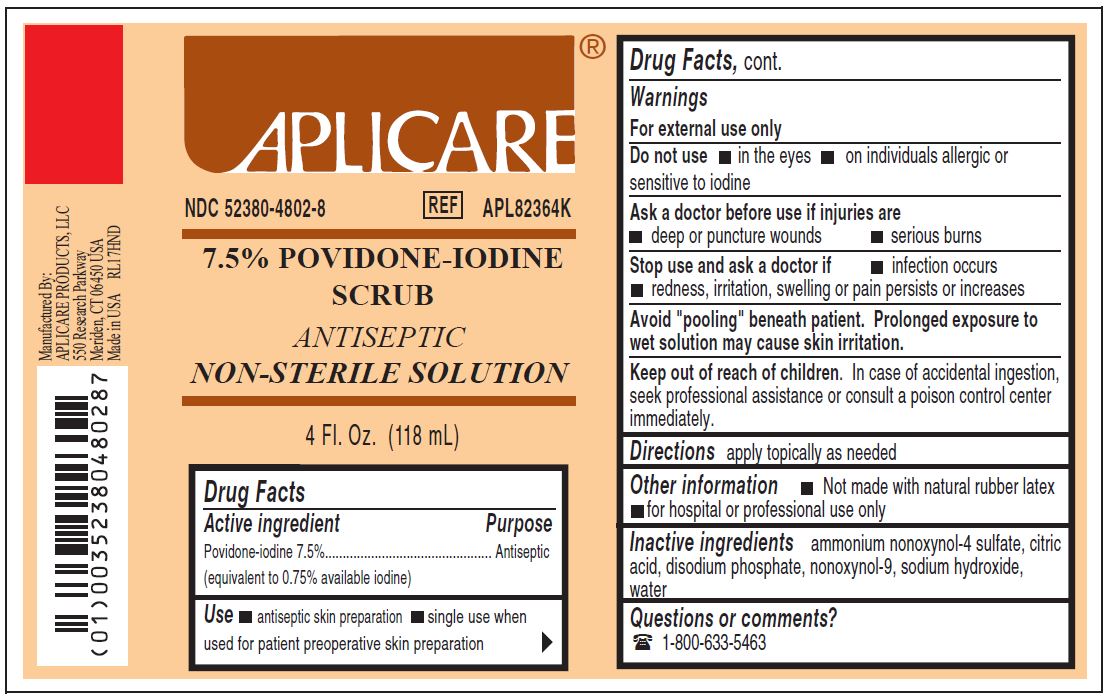 DRUG LABEL: Aplicare Povidone-iodine Scrub
NDC: 52380-4802 | Form: SOLUTION
Manufacturer: Aplicare Products, LLC
Category: otc | Type: HUMAN OTC DRUG LABEL
Date: 20251218

ACTIVE INGREDIENTS: POVIDONE-IODINE 7.5 mg/1 mL
INACTIVE INGREDIENTS: SODIUM PHOSPHATE, DIBASIC; ANHYDROUS CITRIC ACID; SODIUM HYDROXIDE; NONOXYNOL-9; AMMONIUM NONOXYNOL-4 SULFATE; WATER

4802 Povidone-iodine Scrub NonSterile

Active Ingredient

Povidone-iodine 7.5%

Purpose

Antiseptic

Use

- • antiseptic skin preparation
- • single use when used for patient preoperative skin preparation

Warnings

- For external use only
- Avoid "pooling" beneath patient. Prolonged exposure to wet solution may cause skin irritation.

Do not use

- • in the eyes
- • on individuals allergic or sensitive to iodine

Ask a doctor before use if injuries are

- • deep or puncture wounds
- • serious burns

Stop use and ask a doctor if

- • infection occurs
- • redness, irritation, swelling or pain persists or increases

Keep out of reach of children.

In case of accidental ingestion, seek professional assistance or consult a poison control center immediately.

Directions

apply locally as needed

Other information

- • 0.75% titratable iodine
- • not made with natural rubber latex
- • for hospital or professional use only

Inactive ingredients

ammonium nonoxynol-4 sulfate, citric acid, disodium phosphate, nonoxynol-9, sodium hydroxide, water

Questions or comments?

1-800-633-5463

Manufacturing Information

Manufactured by:

Aplicare Products, LLC

550 Research Parkway, Meriden, CT 06450 USA

Manufactured for:

Medline Inustries, LP

Three Lakes Drive, Northfield, IL 60093 USA

Made in USA with domestic and foreign materials

1-800-633-5463

RL17HND

REF: APL82364K